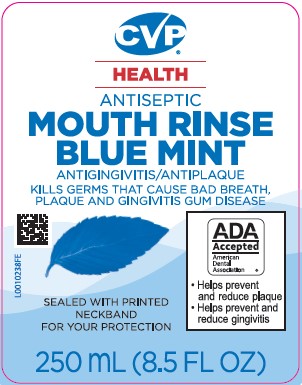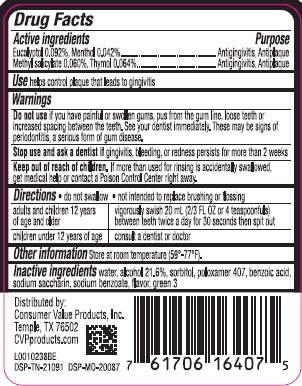 DRUG LABEL: Antispetic
NDC: 57243-664 | Form: MOUTHWASH
Manufacturer: Salado Sales Inc.
Category: otc | Type: HUMAN OTC DRUG LABEL
Date: 20260206

ACTIVE INGREDIENTS: EUCALYPTOL 0.92 mg/1 mL; MENTHOL 0.42 mg/1 mL; METHYL SALICYLATE 0.6 mg/1 mL; THYMOL 0.64 mg/1 mL
INACTIVE INGREDIENTS: WATER; ALCOHOL; SORBITOL; POLOXAMER 407; BENZOIC ACID; SACCHARIN SODIUM; SODIUM BENZOATE; FD&C GREEN NO. 3

CVP 664.003/664AT rev 2 664AU
Blue Mint Antiseptic Mouthrinse

Active ingredients

Eucalyptol 0.092%

Menthol 0.042%

Methyl salicylate 0.060%

Thymol 0.064%

Purpose

Antigingivitis, antiplaque

Use

helps control plaque that leads to gingivitis

Warnings

for this product

Do not use

if you have painful or swollen gums, pus from the gum line, loose teeth or increased spacing between the teeth. See your dentist immediately. These may be signs of periodontitis, a serious form of gum disease.

Stop use and ask a dentist if

gingivitis, bleeding, or redness persists for more than 2 weeks.

Keep out of reach of children.

If more than used for rinsing is accidentally swallowed, get medical help or contact a Poison Control Center right away.

Directions

- do not swallow
- not intended to replace brushing or flossing

adults and children 12 years of age and older - vigorously swish 20 mL (2/3 FL OZ or 4 teaspoonfuls) between teeth twice a day for 30 seconds then spit out

children under 12 years of age - consult a dentist or doctor

Other information

Store at room temperature (59-77).

Inactive ingredients

water, alcohol 21.6%, sorbitol solution, flavor, poloxamer 407, benzoic acid, sodium saccharin, sodium benzoate, FD&C green no.3

Adverse Reactions

Distributed By:

Consumer Value Products, Inc.

Temple, TX 76503

CVPproducts.com

DSP-TN-21091 DSP-MO-20087

principal display panel

CVP®

HEALTH

ANTISEPTIC

MOUTH RINSE

BLUE MINT

ANTIGINGIVITIS/ANTIPLAQUE

KILLS GERMS THAT CAUSE BAD BREATH, PLAQUE AND GINGIVITIS GUM DISEASE

SEALED WITH PRINTED NECKBAND FOR YOUR PROTECTION

ADA Accepted

American Dental Association

- Helps prevent and reduce plaque
- Helps prevent and reduce gingivitis

SEALED WITH PRINTED NECKBAND FOR YOUR PROTECTION

250 mL (8.5 FL OZ)